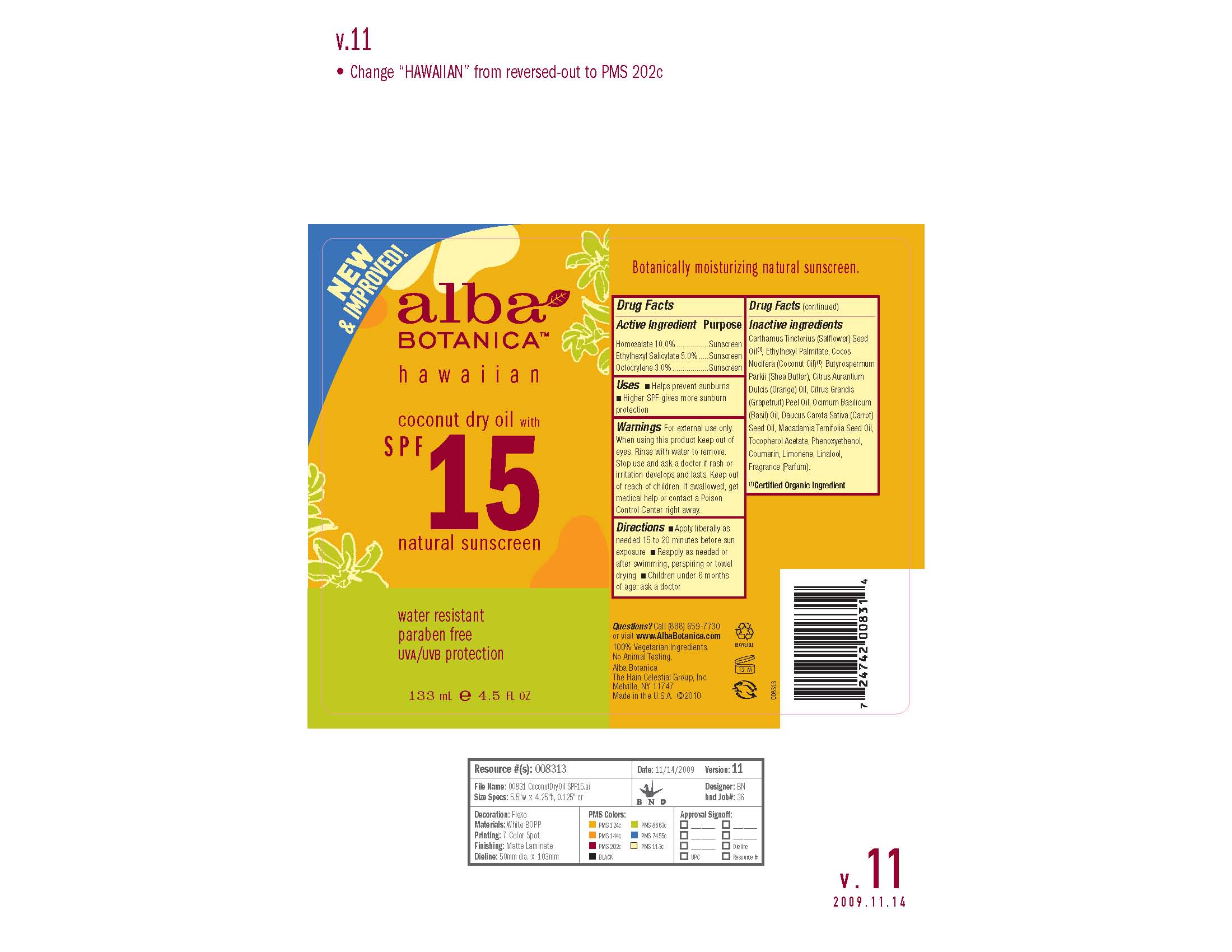 DRUG LABEL: Alba Hawaiian Coconut Siscreen SPF 15
NDC: 61995-2831 | Form: CREAM
Manufacturer: The Hain Celestial Group, Inc.
Category: otc | Type: HUMAN OTC DRUG LABEL
Date: 20100714

ACTIVE INGREDIENTS: Homosalate 10.0 g/100 g; Octisalate 5.0 g/100 g; Octocrylene 3.0 g/100 g

Drug Facts

ACTIVE INGREDIENTS

Homosalate 10.0%

Ethylhexyl Salicilate 5.0%

Octocrylene 3.0%

USES

- Helps prevent sunburns
- Higher SPF gives more sunburn protection

- Apply liberally before sun exposure as needed

- Reapply as needed or after swimming, perspiring or towel drying

- Children under 6 months of age: ask doctor

WARNINGS

For external use only. When using this product keep out of eyes. Rinse with water to remove. Stop use and ask a doctor if rash or irritation develops and lasts. Keep out of reach of children. If swallowed, get medical help or contact Poison Center right away.

QUESTIONS?

Call (888) 659-7730 or visit www.AlbaBotanica.com

100% Vegetarian Ingredients

No Animal Testing

Alba Botanica

The Hain Celestial Group, Inc.

Melville, NY 11747

Made in the U.S.A.